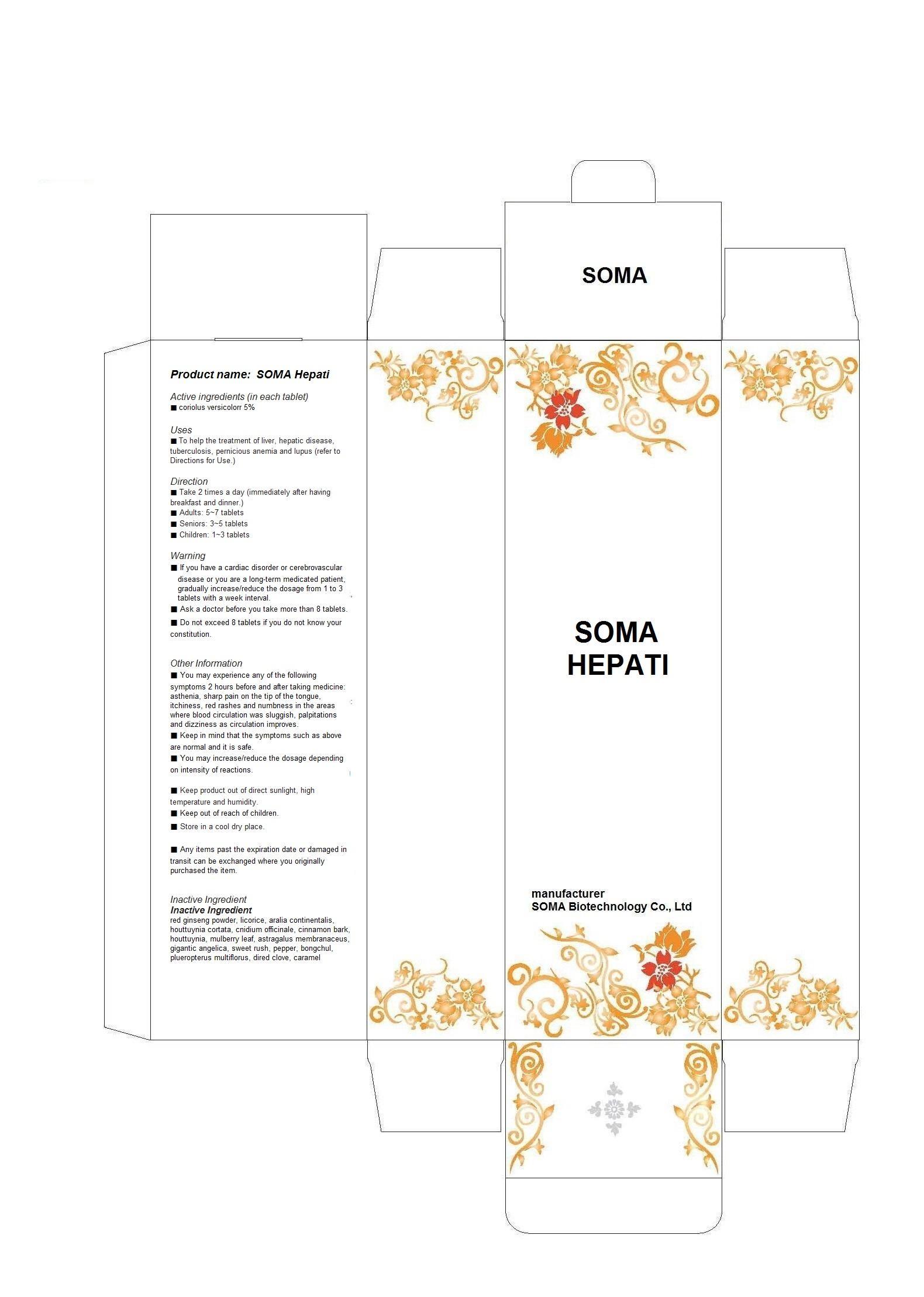 DRUG LABEL: SOMA Hepati
NDC: 58370-9001 | Form: PILL
Manufacturer: SOMA Biotechnology Co., Ltd
Category: otc | Type: HUMAN OTC DRUG LABEL
Date: 20130506

ACTIVE INGREDIENTS: TRAMETES VERSICOLOR FRUITING BODY 0.05 g/1 g
INACTIVE INGREDIENTS: ASIAN GINSENG; GLYCYRRHIZA GLABRA; ARALIA CORDATA ROOT; HOUTTUYNIA CORDATA FLOWERING TOP; CNIDIUM OFFICINALE WHOLE; CINNAMON; MORUS AUSTRALIS LEAF; ASTRAGALUS PROPINQUUS ROOT; ANGELICA SINENSIS ROOT; ACORUS GRAMINEUS ROOT; PEPPERS; ZEDOARY; POLYGONUM CUSPIDATUM WHOLE; CLOVE; CARAMEL

Drug Facts

ACTIVE INGREDIENT

coriolus versicolorr

INACTIVE INGREDIENT

red ginseng powder, licorice, aralia continentalis, houttuynia cortata, cnidium officinale, cinnamon bark, houttuynia, mulberry leaf, astragalus membranaceus, gigantic angelica, sweet rush, pepper, bongchul, plueropterus multiflorus, dired clove, caramel

PURPOSE

To help the treatment of liver, hepatic disease, tuberculosis, pernicious anemia and lupus

keep out of reach of the children

INDICATIONS AND USAGE

- Take 2 times a day
- adults 5~7 pills
- seniors: 3~5 pills
- children: 1~3 pills

WARNINGS

If you have a cardiac disorder or cerebrovascular disease or you are a long-term medicated patient, gradually increase/reduce the dosage from 1 to 3 pills with a week interval.
- Ask a doctor before you take more than 8 pills.
- Do not exceed 8 pills if you do not know your constitution.

DOSAGE AND ADMINISTRATION

for oral use only